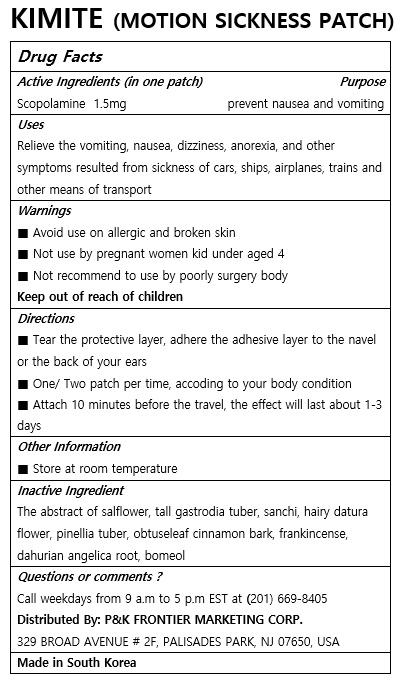 DRUG LABEL: KIMITE
NDC: 72689-0023 | Form: PATCH, EXTENDED RELEASE
Manufacturer: OASIS TRADING
Category: otc | Type: HUMAN OTC DRUG LABEL
Date: 20181212

ACTIVE INGREDIENTS: SCOPOLAMINE 1.5 mg/1 1
INACTIVE INGREDIENTS: DATURA FEROX WHOLE; FRANKINCENSE; ANGELICA DAHURICA ROOT; PINELLIA TERNATA WHOLE; GASTRODIA ELATA TUBER; PANAX NOTOGINSENG ROOT

ACTIVE INGREDIENT

Scopolamine

PURPOSE

Relieve the vomiting, nausea, dizziness, anorexia, and other symptoms resulted from sickness of cars, ships, airplanes, trains and other means of transport

Keep out of reach of children

INDICATIONS AND USAGE

■ Tear the protective layer, adhere the adhesive layer to the navel or the back of your ears

■ One/ Two patch per time, accoding to your body condition

■ Attach 10 minutes before the travel, the effect will last about 1-3 days

WARNINGS

■ Avoid use on allergic and broken skin

■ Not use by pregnant women kid under aged 4

■ Not recommend to use by poorly surgery body

INACTIVE INGREDIENT

The abstract of salflower, tall gastrodia tuber, sanchi, hairy datura flower, pinellia tuber, obtuseleaf cinnamon bark, frankincense, dahurian angelica root, bomeol

DOSAGE AND ADMINISTRATION

For external use only